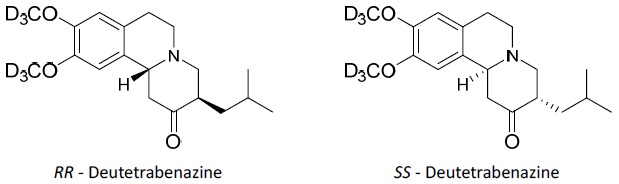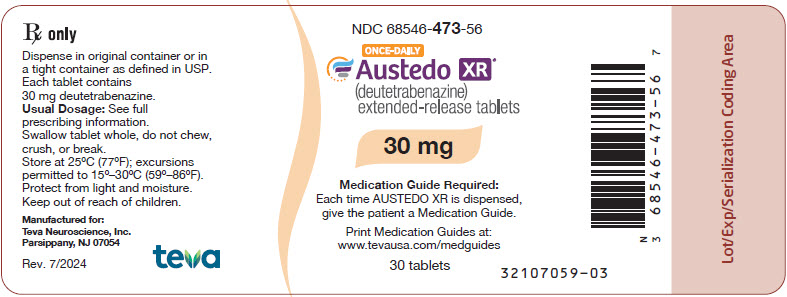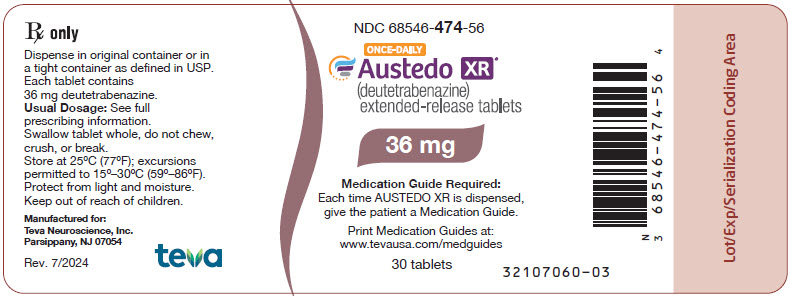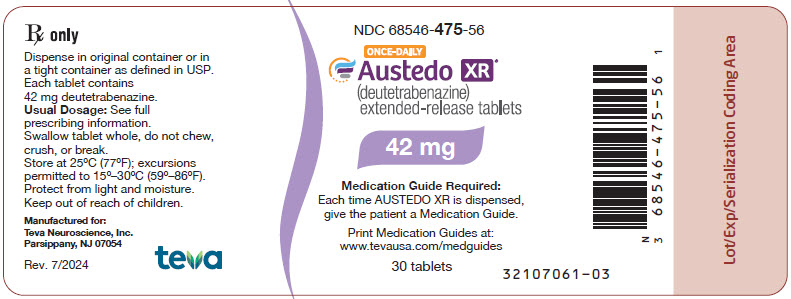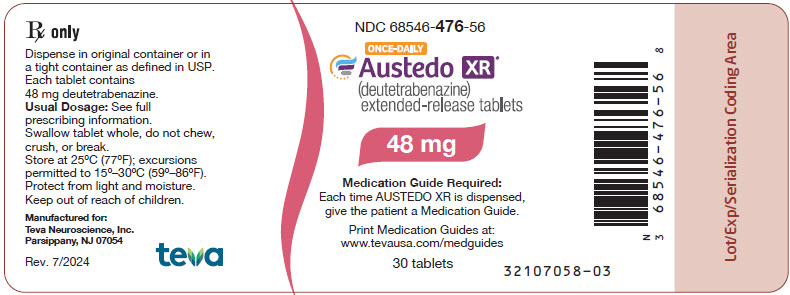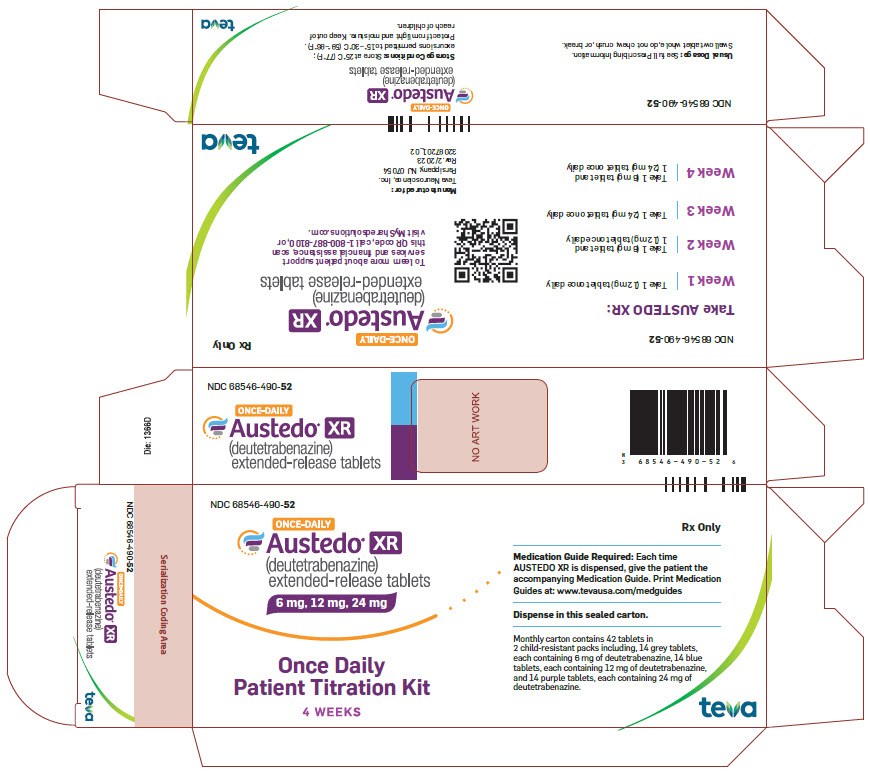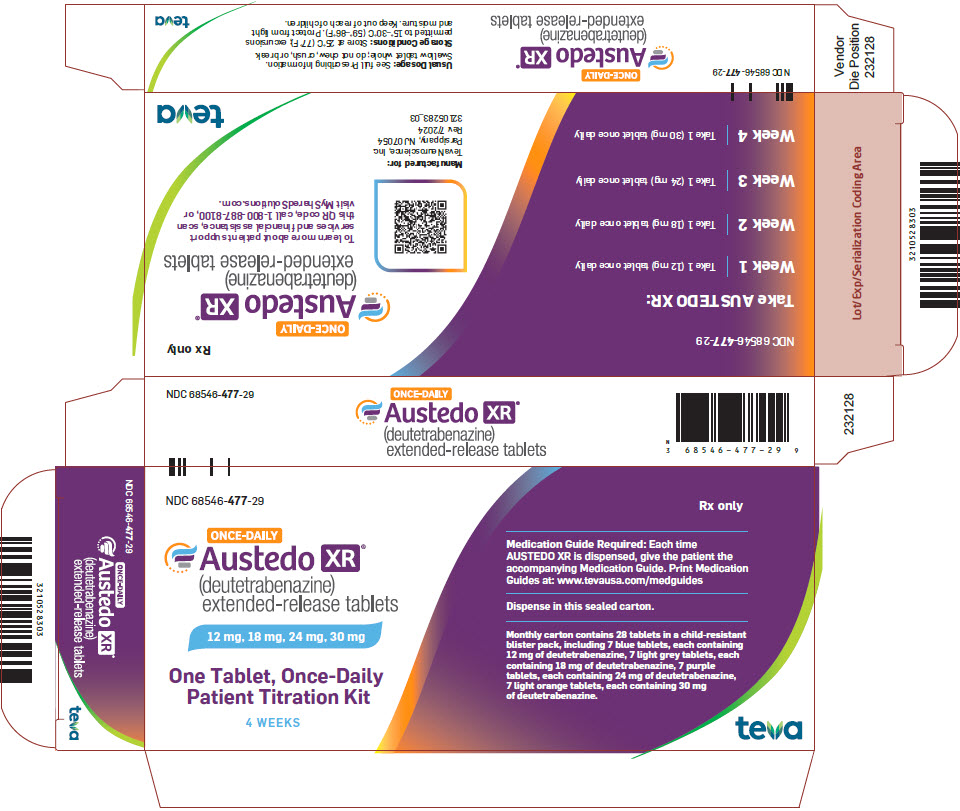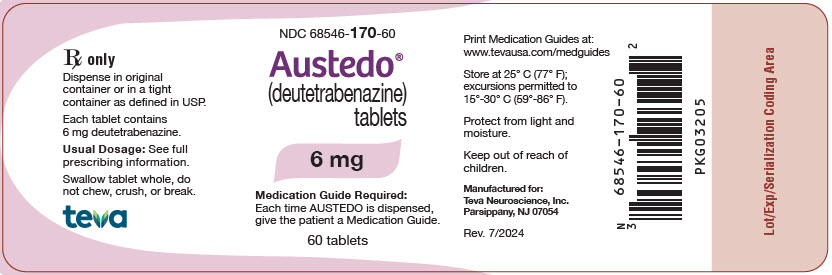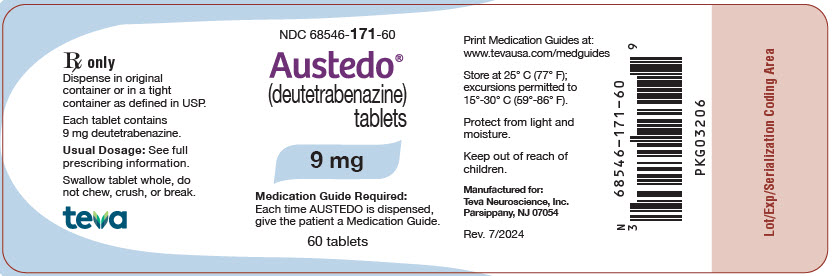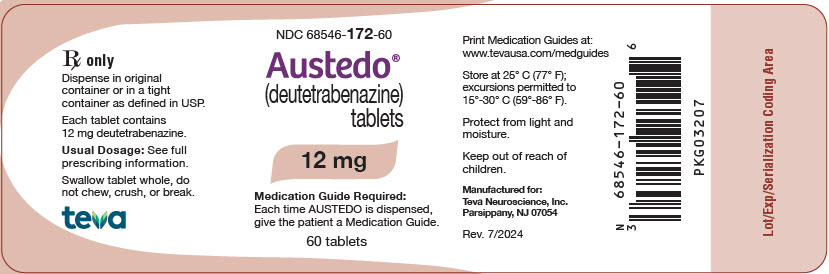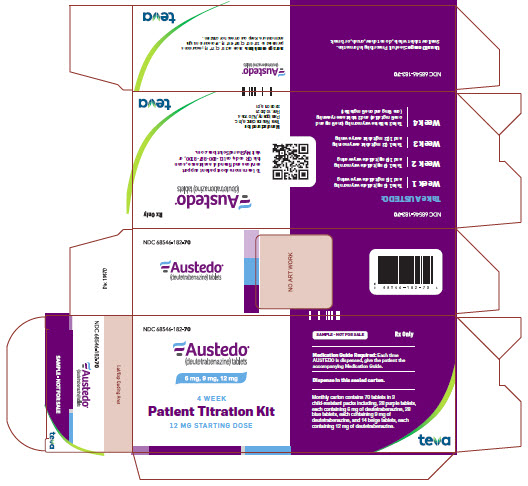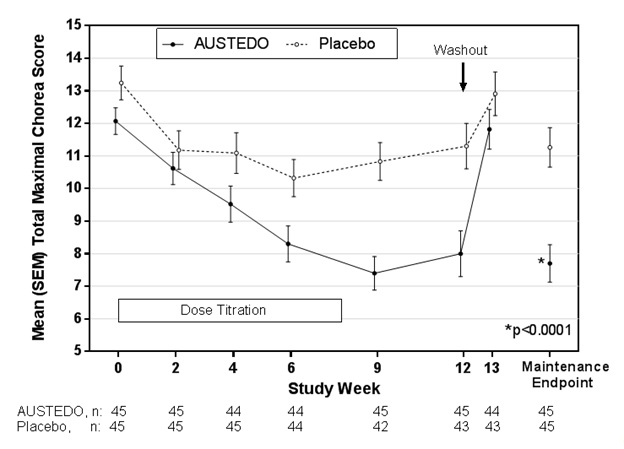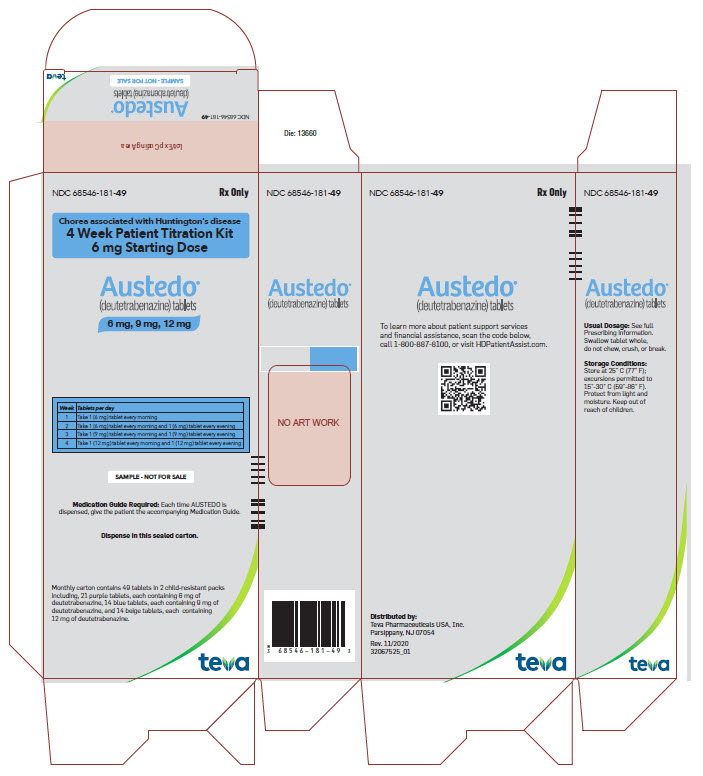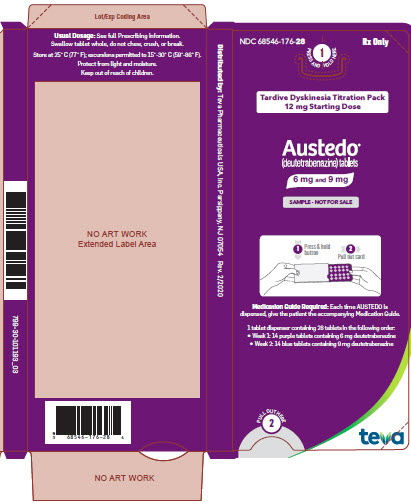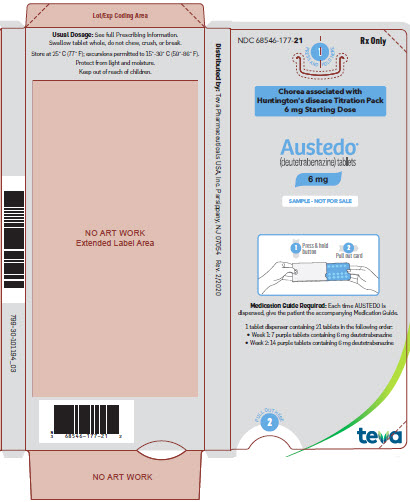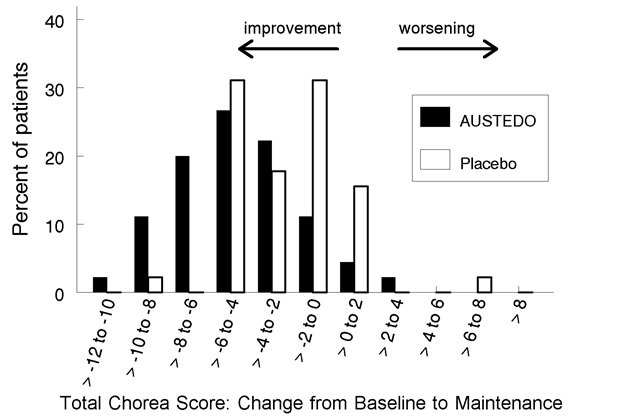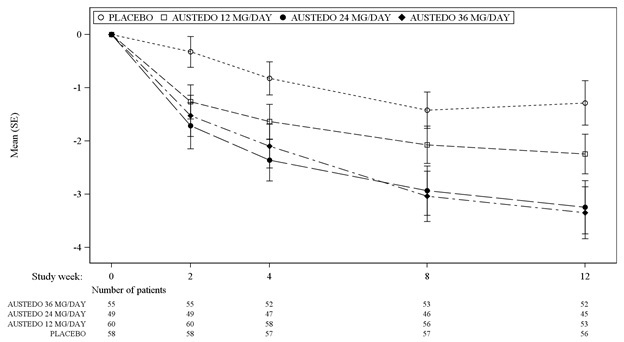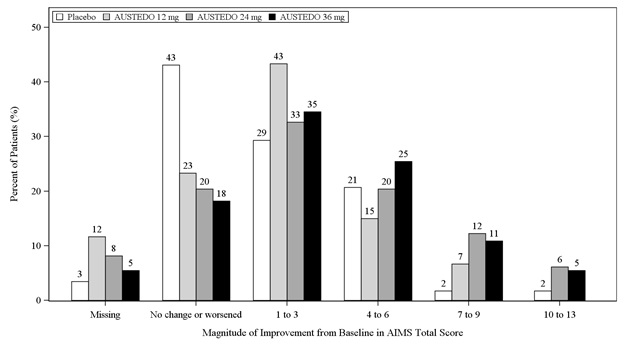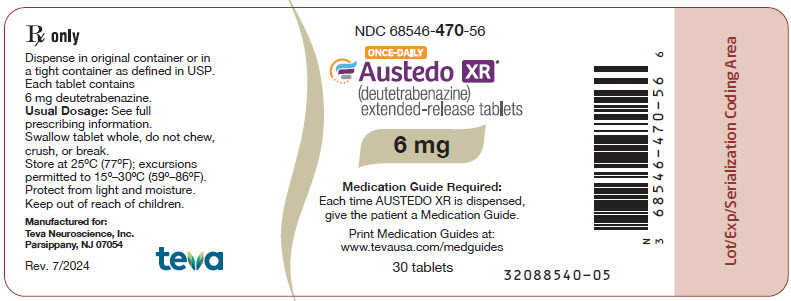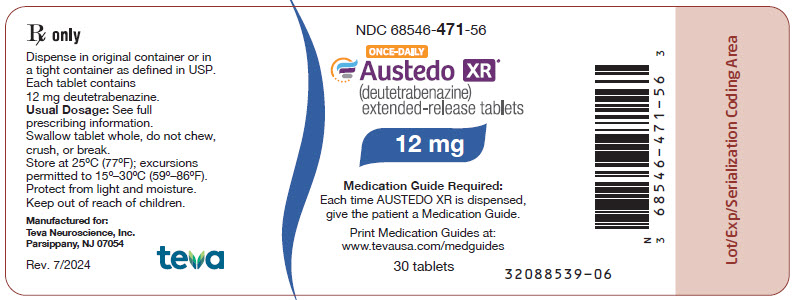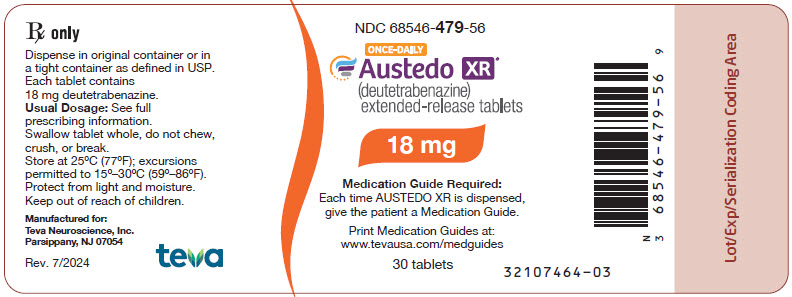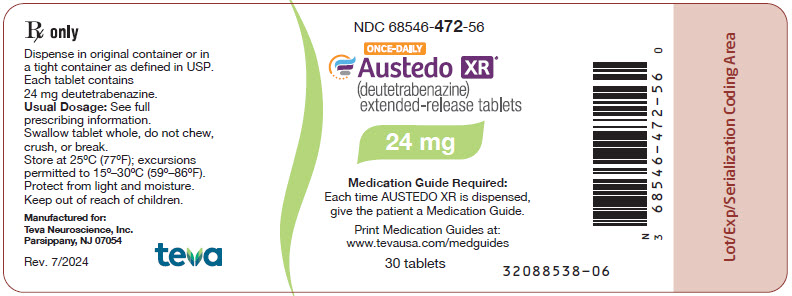 DRUG LABEL: Austedo
NDC: 68546-170 | Form: TABLET, COATED
Manufacturer: Teva Neuroscience, Inc.
Category: prescription | Type: HUMAN PRESCRIPTION DRUG LABEL
Date: 20250228

ACTIVE INGREDIENTS: DEUTETRABENAZINE 6 mg/1 1
INACTIVE INGREDIENTS: AMMONIA; FERROSOFERRIC OXIDE; BUTYL ALCOHOL; BUTYLATED HYDROXYANISOLE; BUTYLATED HYDROXYTOLUENE; MAGNESIUM STEARATE; MANNITOL; MICROCRYSTALLINE CELLULOSE; POLYETHYLENE GLYCOL, UNSPECIFIED; POLYSORBATE 80; POLYVINYL ALCOHOL, UNSPECIFIED; POVIDONE, UNSPECIFIED; PROPYLENE GLYCOL; SHELLAC; TALC; TITANIUM DIOXIDE; FD&C BLUE NO. 2; FD&C RED NO. 40; POLYETHYLENE GLYCOL 2000000

HIGHLIGHTS OF PRESCRIBING INFORMATION

These highlights do not include all the information needed to use AUSTEDO XR or AUSTEDO safely and effectively. See full prescribing information for AUSTEDO XR and AUSTEDO.
AUSTEDO XR® (deutetrabenazine) extended-release tablets, for oral use
AUSTEDO® (deutetrabenazine) tablets, for oral use
Initial U.S. Approval: 2017

WARNING: DEPRESSION AND SUICIDALITY IN PATIENTS WITH HUNTINGTON’S DISEASE

See full prescribing information for complete boxed warning.

- Increases the risk of depression and suicidal thoughts and behavior (suicidality) in patients with Huntington’s disease (5.1)
- Balance risks of depression and suicidality with the clinical need for treatment of chorea when considering the use of AUSTEDO XR or AUSTEDO (5.1)
- Monitor patients for the emergence or worsening of depression, suicidality, or unusual changes in behavior (5.1)
- Inform patients, caregivers, and families of the risk of depression and suicidality and instruct to report behaviors of concern promptly to the treating physician (5.1)
- Exercise caution when treating patients with a history of depression or prior suicide attempts or ideation (5.1)
- AUSTEDO XR and AUSTEDO are contraindicated in patients who are suicidal, and in patients with untreated or inadequately treated depression (4, 5.1)

1 INDICATIONS AND USAGE

AUSTEDO XR and AUSTEDO are vesicular monoamine transporter 2 (VMAT2) inhibitors indicated in adults for the treatment of:

- Chorea associated with Huntington’s disease (1)
- Tardive dyskinesia (1)

2 DOSAGE AND ADMINISTRATION

 | AUSTEDO XR | AUSTEDO
Recommended Starting Dosage | 12 mg once daily (12 mg per day) | 6 mg twice daily (12 mg per day)

- Titrate at weekly intervals by 6 mg per day based on reduction of chorea or tardive dyskinesia, and tolerability, up to a maximum recommended daily dosage of 48 mg (2.1)
- Administer AUSTEDO XR with or without food in once-daily doses (2.1)
- Administer AUSTEDO with food and administer total daily dosages of 12 mg or above in two divided doses (2.1)
- Swallow tablets whole; do not chew, crush, or break (2.1)
- If switching patients from tetrabenazine, discontinue tetrabenazine and initiate AUSTEDO XR or AUSTEDO the following day. See full prescribing information for recommended conversion table (2.2)
- Maximum recommended dosage of AUSTEDO XR or AUSTEDO in poor CYP2D6 metabolizers is 36 mg per day (2.4, 8.7)

3 DOSAGE FORMS AND STRENGTHS

- Extended-release tablets: 6 mg, 12 mg, 18 mg, 24 mg, 30 mg, 36 mg, 42 mg, and 48 mg (3)
- Tablets: 6 mg, 9 mg, and 12 mg (3)

4 CONTRAINDICATIONS

- Suicidal, or untreated/inadequately treated depression in patients with Huntington’s disease (4, 5.1)
- Hepatic impairment (4, 8.6, 12.3)
- Taking reserpine, MAOIs, tetrabenazine, or valbenazine (4, 7.2, 7.3, 7.6)

5 WARNINGS AND PRECAUTIONS

- QT Prolongation: Avoid use in patients with congenital long QT syndrome or with arrhythmias associated with a prolonged QT interval (5.3)
- Neuroleptic Malignant Syndrome (NMS): Discontinue if this occurs (5.4)
- Akathisia, agitation, restlessness, and parkinsonism: Reduce dose or discontinue if this occurs (5.5, 5.6)
- Sedation/somnolence: May impair the patient’s ability to drive or operate complex machinery (5.7)

6 ADVERSE REACTIONS

- Most common adverse reactions (>8% of AUSTEDO-treated patients with Huntington’s disease and greater than placebo): somnolence, diarrhea, dry mouth, and fatigue (6.1)
- Most common adverse reactions (that occurred in 4% of AUSTEDO-treated patients with tardive dyskinesia and greater than placebo): nasopharyngitis and insomnia (6.1)

To report SUSPECTED ADVERSE REACTIONS, contact Teva Pharmaceuticals at 1-888-483-8279 or FDA at 1-800-FDA-1088 or www.fda.gov/medwatch.

7 DRUG INTERACTIONS

- Concomitant use of strong CYP2D6 inhibitors: Maximum recommended dose of AUSTEDO XR or AUSTEDO is 36 mg per day (2.3, 7.1)
- Alcohol or other sedating drugs: May have additive sedation and somnolence (7.5)

8 USE IN SPECIFIC POPULATIONS

Pregnancy: Based on animal data, may cause fetal harm (8.1)

FULL PRESCRIBING INFORMATION

WARNING: DEPRESSION AND SUICIDALITY IN PATIENTS WITH HUNTINGTON’S DISEASE

AUSTEDO XR and AUSTEDO can increase the risk of depression and suicidal thoughts and behavior (suicidality) in patients with Huntington’s disease. Anyone considering the use of AUSTEDO XR or AUSTEDO must balance the risks of depression and suicidality with the clinical need for treatment of chorea. Closely monitor patients for the emergence or worsening of depression, suicidality, or unusual changes in behavior. Patients, their caregivers, and families should be informed of the risk of depression and suicidality and should be instructed to report behaviors of concern promptly to the treating physician.

Particular caution should be exercised in treating patients with a history of depression or prior suicide attempts or ideation, which are increased in frequency in Huntington’s disease. AUSTEDO XR and AUSTEDO are contraindicated in patients who are suicidal, and in patients with untreated or inadequately treated depression [see Contraindications (4) and Warnings and Precautions (5.1)].

1 INDICATIONS AND USAGE

AUSTEDO XR® and AUSTEDO® are indicated in adults for the treatment of:

- chorea associated with Huntington’s disease [see Clinical Studies (14.1)]
- tardive dyskinesia [see Clinical Studies (14.2)]

2 DOSAGE AND ADMINISTRATION

2.1 Dosing Information

The dose of AUSTEDO XR and AUSTEDO is determined individually for each patient based on reduction of chorea or tardive dyskinesia and tolerability. Table 1 displays the recommended dosage and important administration instructions of AUSTEDO XR and AUSTEDO when first prescribed to patients who are not being switched from tetrabenazine (a related VMAT2 inhibitor).

Table 1: Recommended Dosage and Important Administration Instructions for AUSTEDO XR and AUSTEDO

 | AUSTEDO XR extended-release tablet | AUSTEDO tablet
Recommended Starting Dosage | 12 mg once daily (12 mg per day) | 6 mg twice daily (12 mg per day)
Recommended Dose Titration | The dosage of AUSTEDO XR or AUSTEDO may be increased at weekly intervals in increments of 6 mg per day based on reduction of chorea or tardive dyskinesia, and tolerability, up to a maximum recommended daily dosage of 48 mg [see Clinical Trials (14.1, 14.2)].
Important Administration Instructions | - Administer AUSTEDO XR with or without food [see Clinical Pharmacology (12.3)]. - Swallow AUSTEDO XR whole. Do not chew, crush, or break tablets. - Administer AUSTEDO XR once daily. | - Administer AUSTEDO with food [see Clinical Pharmacology (12.3)]. - Swallow AUSTEDO whole. Do not chew, crush, or break tablets. - Administer AUSTEDO total daily dosages of 12 mg or above in two divided doses.
Switching Between AUSTEDO and AUSTEDO XR | When switching between AUSTEDO tablets (twice daily) and AUSTEDO XR extended-release tablets (once daily), switch to the same total daily dosage.

2.2 Switching Patients from Tetrabenazine to AUSTEDO XR or AUSTEDO

Discontinue tetrabenazine and initiate AUSTEDO XR or AUSTEDO the following day. The recommended initial dosing regimen of AUSTEDO XR or AUSTEDO in patients switching from tetrabenazine to AUSTEDO XR or AUSTEDO is shown in Table 2.

Table 2: Recommended Initial Dosing Regimen when Switching from Tetrabenazine to AUSTEDO XR or AUSTEDO

Current tetrabenazine daily dosage | Initial regimen of AUSTEDO XR extended-release tablet | Initial regimen of AUSTEDO tablet
12.5 mg | 6 mg once daily | 6 mg once daily
25 mg | 12 mg once daily | 6 mg twice daily
37.5 mg | 18 mg once daily | 9 mg twice daily
50 mg | 24 mg once daily | 12 mg twice daily
62.5 mg | 30 mg once daily | 15 mg twice daily
75 mg | 36 mg once daily | 18 mg twice daily
87.5 mg | 42 mg once daily | 21 mg twice daily
100 mg | 48 mg once daily | 24 mg twice daily

After patients are switched to AUSTEDO XR or AUSTEDO, the dose may be adjusted at weekly intervals [see Dosage and Administration (2.1)].

2.3 Dosage Adjustment with Strong CYP2D6 Inhibitors

In patients receiving strong CYP2D6 inhibitors, the total daily dosage of AUSTEDO XR or AUSTEDO should not exceed 36 mg [see Drug Interactions (7.1) and Clinical Pharmacology (12.3)].

2.4 Dosage Adjustment in Poor CYP2D6 Metabolizers

In patients who are poor CYP2D6 metabolizers, the total daily dosage of AUSTEDO XR or AUSTEDO should not exceed 36 mg [see Use in Specific Populations (8.7)].

2.5 Discontinuation and Interruption of Treatment

Treatment with AUSTEDO XR or AUSTEDO can be discontinued without tapering. Following treatment interruption of greater than one week, AUSTEDO XR or AUSTEDO therapy should be re-titrated when resumed. For treatment interruption of less than one week, treatment can be resumed at the previous maintenance dose without titration.

3 DOSAGE FORMS AND STRENGTHS

AUSTEDO XR extended-release tablets are available in the following strengths:

- The 6 mg extended-release tablets are round, grey-coated tablets, with “Q6” printed in black ink on one side.
- The 12 mg extended-release tablets are round, blue-coated tablets, with “Q12” printed in black ink on one side.
- The 18 mg extended-release tablets are round, light grey-coated tablets, with “Q18” printed in black ink on one side.
- The 24 mg extended-release tablets are round, purple-coated tablets, with “Q24” printed in black ink on one side.
- The 30 mg extended-release tablets are round, light orange-coated tablets, with “Q30” printed in black ink on one side.
- The 36 mg extended-release tablets are round, light purple-coated tablets, with “Q36” printed in black ink on one side.
- The 42 mg extended-release tablets are round, orange-coated tablets, with “Q42” printed in black ink on one side.
- The 48 mg extended-release tablets are round, pink-coated tablets, with “Q48” printed in black ink on one side.

AUSTEDO tablets are available in the following strengths:

- The 6 mg tablets are round, purple-coated tablets, with “SD” over “6” printed in black ink on one side.
- The 9 mg tablets are round, blue-coated tablets, with “SD” over “9” printed in black ink on one side.
- The 12 mg tablets are round, beige-coated tablets, with “SD” over “12” printed in black ink on one side.

4 CONTRAINDICATIONS

AUSTEDO XR and AUSTEDO are contraindicated in patients:

- With Huntington’s disease who are suicidal, or have untreated or inadequately treated depression [see Warnings and Precautions (5.1)].
- With hepatic impairment [see Use in Specific Populations (8.6), Clinical Pharmacology (12.3)].
- Taking reserpine. At least 20 days should elapse after stopping reserpine before starting AUSTEDO XR or AUSTEDO [see Drug Interactions (7.2)].
- Taking monoamine oxidase inhibitors (MAOIs). AUSTEDO XR and AUSTEDO should not be used in combination with an MAOI, or within 14 days of discontinuing therapy with an MAOI [see Drug Interactions (7.3)].
- Taking tetrabenazine or valbenazine [see Drug Interactions (7.6)].

5 WARNINGS AND PRECAUTIONS

5.1 Depression and Suicidality in Patients with Huntington’s Disease

Patients with Huntington’s disease are at increased risk for depression, and suicidal ideation or behaviors (suicidality). AUSTEDO XR and AUSTEDO may increase the risk for suicidality in patients with Huntington’s disease.

In a 12-week, double-blind, placebo-controlled trial, suicidal ideation was reported by 2% of patients treated with AUSTEDO, compared to no patients on placebo; no suicide attempts and no completed suicides were reported. Depression was reported by 4% of patients treated with AUSTEDO.

When considering the use of AUSTEDO XR or AUSTEDO, the risk of suicidality should be balanced against the need for treatment of chorea. All patients treated with AUSTEDO XR or AUSTEDO should be observed for new or worsening depression or suicidality. If depression or suicidality does not resolve, consider discontinuing treatment with AUSTEDO XR or AUSTEDO.

Patients, their caregivers, and families should be informed of the risks of depression, worsening depression, and suicidality associated with AUSTEDO XR and AUSTEDO, and should be instructed to report behaviors of concern promptly to the treating physician. Patients with Huntington’s disease who express suicidal ideation should be evaluated immediately.

5.2 Clinical Worsening and Adverse Events in Patients with Huntington’s Disease

Huntington’s disease is a progressive disorder characterized by changes in mood, cognition, chorea, rigidity, and functional capacity over time. VMAT2 inhibitors, including AUSTEDO XR and AUSTEDO, may cause a worsening in mood, cognition, rigidity, and functional capacity.

Prescribers should periodically re-evaluate the need for AUSTEDO XR or AUSTEDO in their patients by assessing the effect on chorea and possible adverse effects, including sedation/somnolence, depression and suicidality, parkinsonism, akathisia, restlessness, and cognitive decline. It may be difficult to distinguish between adverse reactions and progression of the underlying disease; decreasing the dose or stopping the drug may help the clinician to distinguish between the two possibilities. In some patients, the underlying chorea itself may improve over time, decreasing the need for AUSTEDO XR or AUSTEDO.

5.3 QTc Prolongation

AUSTEDO XR and AUSTEDO may prolong the QT interval, but the degree of QT prolongation is not clinically significant when AUSTEDO XR or AUSTEDO is administered within the recommended dosage range [see Clinical Pharmacology (12.2)].

AUSTEDO XR and AUSTEDO should be avoided in patients with congenital long QT syndrome and in patients with a history of cardiac arrhythmias. Certain circumstances may increase the risk of the occurrence of torsade de pointes and/or sudden death in association with the use of drugs that prolong the QTc interval, including (1) bradycardia; (2) hypokalemia or hypomagnesemia; (3) concomitant use of other drugs that prolong the QTc interval; and (4) presence of congenital prolongation of the QT interval.

5.4 Neuroleptic Malignant Syndrome (NMS)

A potentially fatal symptom complex sometimes referred to as Neuroleptic Malignant Syndrome (NMS) has been reported in association with drugs that reduce dopaminergic transmission. While NMS has not been observed in patients receiving AUSTEDO XR or AUSTEDO, it has been observed in patients receiving tetrabenazine (a closely related VMAT2 inhibitor). Clinicians should be alerted to the signs and symptoms associated with NMS. Clinical manifestations of NMS are hyperpyrexia, muscle rigidity, altered mental status, and evidence of autonomic instability (irregular pulse or blood pressure, tachycardia, diaphoresis, and cardiac dysrhythmia). Additional signs may include elevated creatinine phosphokinase, myoglobinuria, rhabdomyolysis, and acute renal failure. The diagnosis of NMS can be complicated; other serious medical illness (e.g., pneumonia, systemic infection) and untreated or inadequately treated extrapyramidal disorders can present with similar signs and symptoms. Other important considerations in the differential diagnosis include central anticholinergic toxicity, heat stroke, drug fever, and primary central nervous system pathology.

The management of NMS should include (1) immediate discontinuation of AUSTEDO XR and AUSTEDO; (2) intensive symptomatic treatment and medical monitoring; and (3) treatment of any concomitant serious medical problems for which specific treatments are available. There is no general agreement about specific pharmacological treatment regimens for NMS.

Recurrence of NMS has been reported with resumption of drug therapy. If treatment with AUSTEDO XR or AUSTEDO is needed after recovery from NMS, patients should be monitored for signs of recurrence.

5.5 Akathisia, Agitation, and Restlessness

AUSTEDO XR and AUSTEDO may increase the risk of akathisia, agitation, and restlessness in patients with Huntington’s disease and tardive dyskinesia.

In a 12-week, double-blind, placebo-controlled trial in patients with Huntington’s disease, akathisia, agitation, or restlessness was reported by 4% of patients treated with AUSTEDO, compared to 2% of patients on placebo; in patients with tardive dyskinesia, 2% of patients treated with AUSTEDO and 1% of patients on placebo experienced these events.

Patients receiving AUSTEDO XR or AUSTEDO should be monitored for signs and symptoms of restlessness and agitation, as these may be indicators of developing akathisia. If a patient develops akathisia during treatment with AUSTEDO XR or AUSTEDO, the AUSTEDO XR or AUSTEDO dose should be reduced; some patients may require discontinuation of therapy.

5.6 Parkinsonism

AUSTEDO XR and AUSTEDO may cause parkinsonism in patients with Huntington’s disease or tardive dyskinesia. Parkinsonism has also been observed with other VMAT2 inhibitors.

Because rigidity can develop as part of the underlying disease process in Huntington’s disease, it may be difficult to distinguish between potential drug-induced parkinsonism and progression of underlying Huntington’s disease. Drug-induced parkinsonism has the potential to cause more functional disability than untreated chorea for some patients with Huntington’s disease.

Postmarketing cases of parkinsonism in patients treated with AUSTEDO for tardive dyskinesia have been reported. Signs and symptoms in reported cases have included bradykinesia, gait disturbances, which led to falls in some cases, and the emergence or worsening of tremor. In most cases, the development of parkinsonism occurred within the first two weeks after starting or increasing the dose of AUSTEDO. In cases in which follow-up clinical information was available, parkinsonism was reported to resolve following discontinuation of AUSTEDO therapy.

If a patient develops parkinsonism during treatment with AUSTEDO XR or AUSTEDO, the AUSTEDO XR or AUSTEDO dose should be reduced; some patients may require discontinuation of therapy.

5.7 Sedation and Somnolence

Sedation is a common dose-limiting adverse reaction of AUSTEDO XR and AUSTEDO. In a 12-week, double-blind, placebo-controlled trial examining patients with Huntington’s disease, 11% of AUSTEDO-treated patients reported somnolence compared with 4% of patients on placebo and 9% of AUSTEDO-treated patients reported fatigue compared with 4% of placebo-treated patients.

Patients should not perform activities requiring mental alertness to maintain the safety of themselves or others, such as operating a motor vehicle or operating hazardous machinery, until they are on a maintenance dose of AUSTEDO XR or AUSTEDO and know how the drug affects them.

5.8 Hyperprolactinemia

Serum prolactin levels were not evaluated in the AUSTEDO XR and AUSTEDO development program. Tetrabenazine, a closely related VMAT2 inhibitor, elevates serum prolactin concentrations in humans. Following administration of 25 mg of tetrabenazine to healthy volunteers, peak plasma prolactin levels increased 4- to 5-fold.

Tissue culture experiments indicate that approximately one-third of human breast cancers are prolactin-dependent in vitro, a factor of potential importance if AUSTEDO XR or AUSTEDO is being considered for a patient with previously detected breast cancer. Although amenorrhea, galactorrhea, gynecomastia, and impotence can be caused by elevated serum prolactin concentrations, the clinical significance of elevated serum prolactin concentrations for most patients is unknown.

Chronic increase in serum prolactin levels (although not evaluated in the AUSTEDO XR, AUSTEDO, or tetrabenazine development programs) has been associated with low levels of estrogen and increased risk of osteoporosis. If there is a clinical suspicion of symptomatic hyperprolactinemia, appropriate laboratory testing should be done and consideration should be given to discontinuation of AUSTEDO XR and AUSTEDO.

5.9 Binding to Melanin-Containing Tissues

Since deutetrabenazine or its metabolites bind to melanin-containing tissues, it could accumulate in these tissues over time. This raises the possibility that AUSTEDO XR and AUSTEDO may cause toxicity in these tissues after extended use. Neither ophthalmologic nor microscopic examination of the eye has been conducted in the chronic toxicity studies in a pigmented species such as dogs. Ophthalmologic monitoring in humans was inadequate to exclude the possibility of injury occurring after long-term exposure.

The clinical relevance of deutetrabenazine’s binding to melanin-containing tissues is unknown. Although there are no specific recommendations for periodic ophthalmologic monitoring, prescribers should be aware of the possibility of long-term ophthalmologic effects [see Clinical Pharmacology (12.2)].

6 ADVERSE REACTIONS

The following serious adverse reactions are discussed in greater detail in other sections of the labeling:

- Depression and Suicidality in Patients with Huntington’s disease [see Warnings and Precautions (5.1)]
- QTc Prolongation [see Warnings and Precautions (5.3)]
- Neuroleptic Malignant Syndrome (NMS) [see Warnings and Precautions (5.4)]
- Akathisia, Agitation, and Restlessness [see Warnings and Precautions (5.5)]
- Parkinsonism [see Warnings and Precautions (5.6)]
- Sedation and Somnolence [see Warnings and Precautions (5.7)]
- Hyperprolactinemia [see Warnings and Precautions (5.8)]
- Binding to Melanin-Containing Tissues [see Warnings and Precautions (5.9)]

6.1 Clinical Trials Experience

Because clinical trials are conducted under widely varying conditions, adverse reaction rates observed in the clinical trials of a drug cannot be directly compared to rates in the clinical trials of another drug and may not reflect the rates observed in practice.

The studies described below were conducted with AUSTEDO tablets; adverse reactions with AUSTEDO XR extended-release tablets are expected to be similar to AUSTEDO tablets.

Patients with Huntington’s Disease

Study 1 [see Clinical Studies (14.1)] was a randomized, 12-week, placebo-controlled study in patients with chorea associated with Huntington’s disease. A total of 45 patients received AUSTEDO, and 45 patients received placebo. Patients ranged in age between 23 and 74 years (mean 54 years); 56% were male, and 92% were Caucasian. The most common adverse reactions occurring in greater than 8% of AUSTEDO-treated patients were somnolence, diarrhea, dry mouth, and fatigue. Adverse reactions occurring in 4% or more of patients treated with AUSTEDO, and with a greater incidence than in patients on placebo, are summarized in Table 3.

Table 3: Adverse Reactions in Patients with Huntington's Disease (Study 1) Experienced by at Least 4% of Patients on AUSTEDO and with a Greater Incidence than on Placebo

Adverse Reaction | AUSTEDO (N = 45) % | Placebo (N = 45) %
Somnolence | 11 | 4
Diarrhea | 9 | 0
Dry mouth | 9 | 7
Fatigue | 9 | 4
Urinary tract infection | 7 | 2
Insomnia | 7 | 4
Anxiety | 4 | 2
Constipation | 4 | 2
Contusion | 4 | 2

One or more adverse reactions resulted in a reduction of the dose of study medication in 7% of patients in Study 1. The most common adverse reaction resulting in dose reduction in patients receiving AUSTEDO was dizziness (4%).

Agitation led to discontinuation in 2% of patients treated with AUSTEDO in Study 1.

Patients with Tardive Dyskinesia

The data described below reflect 410 tardive dyskinesia patients participating in clinical trials. AUSTEDO was studied primarily in two 12-week, placebo-controlled trials (fixed dose, dose escalation) [see Clinical Studies (14.2)]. The population was 18 to 80 years of age, and had tardive dyskinesia and had concurrent diagnoses of mood disorder (33%) or schizophrenia/schizoaffective disorder (63%). In these studies, AUSTEDO was administered in doses ranging from 12-48 mg per day. All patients continued on previous stable regimens of antipsychotics; 71% and 14% respective atypical and typical antipsychotic medications at study entry.

The most common adverse reactions occurring in greater than 3% of AUSTEDO-treated patients and greater than placebo were nasopharyngitis and insomnia. The adverse reactions occurring in >2% or more patients treated with AUSTEDO (12-48 mg per day) and greater than in placebo patients in two double-blind, placebo-controlled studies in patients with tardive dyskinesia (Study 1 and Study 2) are summarized in Table 4.

Table 4: Adverse Reactions in 2 Placebo-Controlled Tardive Dyskinesia Studies (Study 1 and Study 2) of 12-week Treatment on AUSTEDO Reported in at Least 2% of Patients and Greater than Placebo

Adverse Reaction | AUSTEDO (N=279) (%) | Placebo (N=131) (%)
Nasopharyngitis | 4 | 2
Insomnia | 4 | 1
Depression/ Dysthymic disorder | 2 | 1
Akathisia/Agitation/Restlessness | 2 | 1

One or more adverse reactions resulted in a reduction of the dose of study medication in 4% of AUSTEDO-treated patients and in 2% of placebo-treated patients.

7 DRUG INTERACTIONS

7.1 Strong CYP2D6 Inhibitors

A reduction in AUSTEDO XR or AUSTEDO dose may be necessary when adding a strong CYP2D6 inhibitor in patients maintained on a stable dose of AUSTEDO XR or AUSTEDO. Concomitant use of strong CYP2D6 inhibitors (e.g., paroxetine, fluoxetine, quinidine, bupropion) has been shown to increase the systemic exposure to the active dihydro-metabolites of deutetrabenazine by approximately 3-fold. The daily dose of AUSTEDO XR or AUSTEDO should not exceed 36 mg per day in patients taking strong CYP2D6 inhibitors [see Dosage and Administration (2.3) and Clinical Pharmacology (12.3)].

7.2 Reserpine

Reserpine binds irreversibly to VMAT2 and the duration of its effect is several days. Prescribers should wait for chorea or dyskinesia to reemerge before administering AUSTEDO XR or AUSTEDO to help reduce the risk of overdosage and major depletion of serotonin and norepinephrine in the central nervous system. At least 20 days should elapse after stopping reserpine before starting AUSTEDO XR or AUSTEDO. AUSTEDO XR and AUSTEDO should not be used concomitantly with reserpine [see Contraindications (4)].

7.3 Monoamine Oxidase Inhibitors (MAOIs)

AUSTEDO XR and AUSTEDO are contraindicated in patients taking MAOIs. AUSTEDO XR and AUSTEDO should not be used in combination with an MAOI, or within 14 days of discontinuing therapy with an MAOI [see Contraindications (4)].

7.4 Neuroleptic Drugs

The risk of parkinsonism, NMS, and akathisia may be increased by concomitant use of AUSTEDO XR or AUSTEDO with dopamine antagonists or antipsychotics.

7.5 Alcohol or Other Sedating Drugs

Concomitant use of alcohol or other sedating drugs may have additive effects and worsen sedation and somnolence [see Warnings and Precautions (5.7)].

7.6 Concomitant Tetrabenazine or Valbenazine

AUSTEDO XR and AUSTEDO are contraindicated in patients currently taking tetrabenazine or valbenazine. AUSTEDO XR or AUSTEDO may be initiated the day following discontinuation of tetrabenazine [see Dosage and Administration (2.2)].

8 USE IN SPECIFIC POPULATIONS

8.1 Pregnancy

Risk Summary

There are no adequate data on the developmental risk associated with the use of AUSTEDO XR or AUSTEDO in pregnant women. Administration of deutetrabenazine to rats during organogenesis produced no clear adverse effect on embryofetal development. However, administration of tetrabenazine to rats throughout pregnancy and lactation resulted in an increase in stillbirths and postnatal offspring mortality [see Data].

In the U.S. general population, the estimated background risk of major birth defects and miscarriage in clinically recognized pregnancies is 2-4% and 15-20%, respectively. The background risk of major birth defects and miscarriage for the indicated population is unknown.

Data

Animal Data

Oral administration of deutetrabenazine (5, 10, or 30 mg/kg/day) or tetrabenazine (30 mg/kg/day) to pregnant rats during organogenesis had no clear effect on embryofetal development. The highest dose tested was 6 times the maximum recommended human dose of 48 mg/day, on a body surface area (mg/m^2) basis.

The effects of deutetrabenazine when administered during organogenesis to rabbits or during pregnancy and lactation to rats have not been assessed.

Tetrabenazine had no effects on embryofetal development when administered to pregnant rabbits during the period of organogenesis at oral doses up to 60 mg/kg/day. When tetrabenazine was administered to female rats (doses of 5, 15, and 30 mg/kg/day) from the beginning of organogenesis through the lactation period, an increase in stillbirths and offspring postnatal mortality was observed at 15 and 30 mg/kg/day, and delayed pup maturation was observed at all doses.

8.2 Lactation

Risk Summary

There are no data on the presence of deutetrabenazine or its metabolites in human milk, the effects on the breastfed infant, or the effects of the drug on milk production.

The developmental and health benefits of breastfeeding should be considered along with the mother’s clinical need for AUSTEDO XR or AUSTEDO and any potential adverse effects on the breastfed infant from AUSTEDO XR or AUSTEDO or from the underlying maternal condition.

8.4 Pediatric Use

Chorea associated with Huntington’s Disease and Tardive Dyskinesia

The safety and effectiveness of AUSTEDO XR and AUSTEDO have not been established in pediatric patients for the treatment of chorea associated with Huntington’s disease or for the treatment of tardive dyskinesia.

Tourette Syndrome

The safety and effectiveness of AUSTEDO XR and AUSTEDO have not been established in pediatric patients for the treatment of Tourette syndrome.

Efficacy was not demonstrated in two randomized, double-blind, placebo-controlled studies in pediatric patients aged 6 to 16 years with Tourette syndrome. One study evaluated fixed doses of deutetrabenazine over 8 weeks (NCT03571256); the other evaluated flexible doses of deutetrabenazine over 12 weeks (NCT03452943). The studies included a total of 274 pediatric patients who received at least one dose of deutetrabenazine or placebo. The primary efficacy endpoint in both studies was the change from baseline to end-of-treatment on the Yale Global Tic Severity Scale Total Tic Score (YGTSS-TTS). The estimated treatment effect of deutetrabenazine on the YGTSS-TTS was not statistically significantly different from placebo in either study. The placebo subtracted least squares means difference in YGTSS-TTS from baseline to end-of-treatment was -0.7 (95% CI: -4.1, 2.8) in the flexible dose study and -0.8 (95% CI: -3.9, 2.3) for the primary analysis in the fixed dose study.

The following adverse reactions were reported in frequencies of at least 5% of pediatric patients treated with AUSTEDO and with a greater incidence than in pediatric patients receiving placebo (AUSTEDO vs placebo): headache (includes: migraine, migraine with aura, and headache; 13% vs 9%), somnolence (includes: sedation, hypersomnia, and somnolence; 11% vs 2%), fatigue (8% vs 3%), increased appetite (5% vs <1%), and increased weight (5% vs <1%).

Juvenile Animal Toxicity Data

Deutetrabenazine orally administered to juvenile rats from postnatal days 21 through 70 (at 2.5, 5, or 10 mg/kg/day) resulted in an increased incidence of tremor, hyperactivity, and adverse increases in motor activity at ≥5 mg/kg/day, and reduced body weight and food consumption at 10 mg/kg/day. There was no reproductive or early embryonic toxicity up to the highest dose. All drug-related findings were reversible after a drug-free period. The no observed adverse effect level (NOAEL) in juvenile rats was 2.5 mg/kg/day. These drug-related findings were similar to those observed in adult rats; however, the juvenile rats were more sensitive.

8.5 Geriatric Use

Clinical studies of AUSTEDO XR and AUSTEDO did not include sufficient numbers of subjects aged 65 and over to determine whether they respond differently from younger subjects. Other reported clinical experience has not identified differences in responses between the elderly and younger patients. In general, dose selection for an elderly patient should be cautious, usually starting at the low end of the dosing range, reflecting the greater frequency of hepatic, renal, and cardiac dysfunction, and of concomitant disease or other drug therapy.

8.6 Hepatic Impairment

The effect of hepatic impairment on the pharmacokinetics of deutetrabenazine and its primary metabolites has not been studied; however, in a clinical study conducted with tetrabenazine, a closely related VMAT2 inhibitor, there was a large increase in exposure to tetrabenazine and its active metabolites in patients with hepatic impairment. The clinical significance of this increased exposure has not been assessed, but because of concerns for a greater risk for serious adverse reactions, the use of AUSTEDO XR or AUSTEDO in patients with hepatic impairment is contraindicated [see Contraindications (4), Clinical Pharmacology (12.3)].

8.7 Poor CYP2D6 Metabolizers

Although the pharmacokinetics of deutetrabenazine and its metabolites have not been systematically evaluated in patients who do not express the drug metabolizing enzyme, it is likely that the exposure to α-HTBZ and β-HTBZ would be increased similarly to taking a strong CYP2D6 inhibitor (approximately 3-fold). In patients who are CYP2D6 poor metabolizers, the daily dose of AUSTEDO XR or AUSTEDO should not exceed 36 mg [see Dosage and Administration (2.4) and Clinical Pharmacology (12.3)].

10 OVERDOSAGE

Overdoses ranging from 100 mg to 1 g have been reported in the literature with tetrabenazine, a closely related VMAT2 inhibitor. The following adverse reactions occurred with overdosing: acute dystonia, oculogyric crisis, nausea and vomiting, sweating, sedation, hypotension, confusion, diarrhea, hallucinations, rubor, and tremor.

Treatment should consist of those general measures employed in the management of overdosage with any central nervous system-active drug. General supportive and symptomatic measures are recommended. Cardiac rhythm and vital signs should be monitored. In managing overdosage, the possibility of multiple drug involvement should always be considered. The physician should consider contacting a poison control center on the treatment of any overdose. Telephone numbers for certified poison control centers are listed on the American Association of Poison Control Centers website www.aapcc.org.

11 DESCRIPTION

AUSTEDO XR extended-release tablets and AUSTEDO tablets are formulated with deutetrabenazine, a vesicular monoamine transporter 2 (VMAT2) inhibitor for oral administration. The molecular weight of deutetrabenazine is 323.46; the pKa is 6.31. Deutetrabenazine is a hexahydro-dimethoxybenzoquinolizine derivative and has the following chemical name: (RR, SS)-1, 3, 4, 6, 7, 11b-hexahydro-9, 10-di(methoxy-d3)-3-(2-methylpropyl)-2H-benzo[a]quinolizin-2-one.

The molecular formula for deutetrabenazine is C19H21D6NO3. Deutetrabenazine is a racemic mixture containing the following structures:

Deutetrabenazine is a white to slightly yellow crystalline powder that is sparingly soluble in water and soluble in ethanol.
AUSTEDO XR

AUSTEDO XR extended-release tablets contain 6 mg, 12 mg, 18 mg, 24 mg, 30 mg, 36 mg, 42 mg, or 48 mg deutetrabenazine, and the following inactive ingredients: ammonium hydroxide, black iron oxide, butyl alcohol, butylated hydroxyanisole, butylated hydroxytoluene, cellulose acetate, hydroxypropyl cellulose, hypromellose, isopropyl alcohol, magnesium stearate, polyethylene glycol, polyethylene glycol 3350, polyethylene oxide, polyvinyl alcohol, propylene glycol, shellac, sodium chloride, talc, titanium dioxide, and FD&C red #40 lake. The 6 mg, 12 mg, 18 mg, 30 mg, 36 mg, and 42 mg extended-release tablets also contain FD&C yellow #6 lake. The 6 mg, 12 mg, 24 mg, and 36 mg extended-release tablets also contain FD&C blue #2 lake. The 18 mg extended-release tablets also contain carmine.
AUSTEDO XR Delivery System Components and Performance
AUSTEDO XR uses osmotic pressure to deliver deutetrabenazine at a controlled rate. The delivery system, which resembles a round tablet in appearance, consists of a bilayer core tablet that contains deutetrabenazine along with other excipients. The biologically inert components of the tablet remain intact during gastrointestinal transit and are eliminated in the stool.

AUSTEDO

AUSTEDO tablets contain 6 mg, 9 mg, or 12 mg deutetrabenazine, and the following inactive ingredients: ammonium hydroxide, black iron oxide, butyl alcohol, butylated hydroxyanisole, butylated hydroxytoluene, magnesium stearate, mannitol, microcrystalline cellulose, polyethylene glycol, polyethylene oxide, polysorbate 80, polyvinyl alcohol, povidone, propylene glycol, shellac, talc, titanium dioxide, and FD&C blue #2 lake. The 6 mg tablets also contain FD&C red #40 lake. The 12 mg tablets also contain FD&C yellow #6 lake.

12 CLINICAL PHARMACOLOGY

12.1 Mechanism of Action

The precise mechanism by which deutetrabenazine exerts its effects in the treatment of tardive dyskinesia and chorea in patients with Huntington’s disease is unknown but is believed to be related to its effect as a reversible depletor of monoamines (such as dopamine, serotonin, norepinephrine, and histamine) from nerve terminals. The major circulating metabolites (α-dihydrotetrabenazine [HTBZ] and β-HTBZ) of deutetrabenazine, are reversible inhibitors of VMAT2, resulting in decreased uptake of monoamines into synaptic vesicles and depletion of monoamine stores.

12.2 Pharmacodynamics

Cardiac Electrophysiology

At the maximum recommended dose, AUSTEDO XR and AUSTEDO do not prolong the QT interval to any clinically relevant extent. An exposure-response analysis on QTc prolongation from a study in extensive or intermediate (EM) and poor CYP2D6 metabolizers (PM) showed that a clinically-relevant effect can be excluded at exposures following single doses of 24 and 48 mg of AUSTEDO.

Melanin Binding

Deutetrabenazine or its metabolites bind to melanin-containing tissues (i.e., eye, skin, fur) in pigmented rats. After a single oral dose of radiolabeled deutetrabenazine, radioactivity was still detected in eye and fur at 35 days following dosing [see Warnings and Precautions (5.9)].

12.3 Pharmacokinetics

After oral dosing, plasma concentrations of deutetrabenazine are low compared to that of the active deuterated metabolites because of the extensive hepatic metabolism of deutetrabenazine.

AUSTEDO XR

Systemic exposure (i.e., peak plasma concentrations [Cmax] and the area under the plasma concentration-time curve [AUC]) for deutetrabenazine and the active, deuterated dihydro metabolites (HTBZ), α-HTBZ and β-HTBZ, increased proportionally to dose following single doses of AUSTEDO XR over the recommended clinical dosage range (6 mg to 48 mg).

AUSTEDO

Systemic exposure (Cmax and AUC) for the active metabolites increased proportionally to dose following single or multiple doses of deutetrabenazine (6 mg to 24 mg and 7.5 mg twice daily to 22.5 mg twice daily).

Absorption

Following oral administration of deutetrabenazine, the extent of absorption is at least 80%.

AUSTEDO XR

Peak plasma concentrations (Cmax) of deutetrabenazine, deuterated α-HTBZ, and β-HTBZ are reached within approximately 3 hours, followed by sustained plateaus for several hours allowing for a 24-hour dosing interval.

AUSTEDO

Peak plasma concentrations (Cmax) of deutetrabenazine, deuterated α-HTBZ and β-HTBZ are reached within 3 to 4 hours after dosing.

Effect of Food

AUSTEDO XR

The effects of food on the bioavailability of AUSTEDO XR were studied in subjects administered a single dose with and without food. Food had no effect on Cmax or AUC of deutetrabenazine, α-HTBZ or β-HTBZ [see Dosage and Administration (2.1)].

AUSTEDO

The effects of food on the bioavailability of AUSTEDO were studied in subjects administered a single dose with and without food. Food had no effect on AUC of α-HTBZ or β-HTBZ, although Cmax was increased by approximately 50% in the presence of food [see Dosage and Administration (2.1)].

Distribution

The median volume of distribution (Vc/F) of the α-HTBZ, and the β-HTBZ metabolites of deutetrabenazine are approximately 500 L and 730 L, respectively.

Results of PET-scan studies in humans show that following intravenous injection of ^11C-labeled tetrabenazine or α-HTBZ, radioactivity is rapidly distributed to the brain, with the highest binding in the striatum and lowest binding in the cortex.

The protein binding of deutetrabenazine and deuterated α-HTBZ and β-HTBZ in human plasma at the concentration of 0.1 µM is 82%, 57%, and 49% respectively, with no preferential binding of drug-related total radioactivity to the cellular components of human blood.

Elimination

AUSTEDO XR and AUSTEDO are primarily renally eliminated in the form of metabolites.

The half-life of the active deuterated α-HTBZ, β-HTBZ, and total (α+β)-HTBZ metabolites is approximately 12 hours, 7.5 hours, and 9 to 11 hours, respectively.

The clearance values (CL/F) of the α-HTBZ, and β-HTBZ metabolites of AUSTEDO are approximately 65 L/hour and 200 L/hour, respectively, for a 70 kg HD or TD patient with functional CYP2D6 metabolism in the fed state.

The elimination half-life and clearance of AUSTEDO XR are similar to that of AUSTEDO.

Metabolism

In vitro experiments in human liver microsomes demonstrate that deutetrabenazine is extensively biotransformed, mainly by carbonyl reductase, to its major active metabolites, α-HTBZ and β-HTBZ, which are subsequently metabolized primarily by CYP2D6, with minor contributions of CYP1A2 and CYP3A4/5, to form several minor metabolites.

Excretion

In a mass balance study in 6 healthy subjects, 75% to 86% of the deutetrabenazine dose was excreted in the urine, and fecal recovery accounted for 8% to 11% of the dose. Urinary excretion of the α-HTBZ and β-HTBZ metabolites from deutetrabenazine each accounted for less than 10% of the administered dose. Sulfate and glucuronide conjugates of the α-HTBZ and β-HTBZ metabolites of deutetrabenazine, as well as products of oxidative metabolism, accounted for the majority of metabolites in the urine.

Specific Populations

Male and Female Patients

There is no apparent effect of gender on the pharmacokinetics of α-HTBZ and β‑HTBZ of deutetrabenazine.

Patients with Renal Impairment

No clinical studies have been conducted to assess the effect of renal impairment on the PK of deutetrabenazine and its primary metabolites.

Patients with Hepatic Impairment

The effect of hepatic impairment on the pharmacokinetics of deutetrabenazine and its primary metabolites has not been studied. However, in a clinical study conducted to assess the effect of hepatic impairment on the pharmacokinetics of tetrabenazine, a closely related VMAT2 inhibitor, the exposure to α-HTBZ and β-HTBZ was up to 40% greater in patients with hepatic impairment, and the mean tetrabenazine Cmax in patients with hepatic impairment was up to 190-fold higher than in healthy subjects [see Contraindications (4), Use in Specific Populations (8.6)].

Poor CYP2D6 Metabolizers

Although the pharmacokinetics of deutetrabenazine and its metabolites have not been systematically evaluated in patients who do not express the drug metabolizing enzyme CYP2D6, it is likely that the exposure to α-HTBZ and β-HTBZ would be increased similarly to taking strong CYP2D6 inhibitors (approximately 3-fold) [see Dosage and Administration (2.4), Drug Interactions (7.1)].

Drug Interaction Studies

Effect of Other Drugs on AUSTEDO/AUSTEDO XR

CYP2D6 Inhibitors

In vitro studies indicate that the α-HTBZ and β-HTBZ metabolites of deutetrabenazine are substrates for CYP2D6. The effect of CYP2D6 inhibition on the pharmacokinetics of deutetrabenazine and its metabolites was studied in 24 healthy subjects following a single 22.5 mg dose of deutetrabenazine given after 8 days of administration of the strong CYP2D6 inhibitor paroxetine 20 mg daily. In the presence of paroxetine, systemic exposure (AUCinf) of α-HTBZ was 1.9-fold higher and β-HTBZ was 6.5-fold higher, resulting in approximately 3-fold increase in AUCinf for total (α+β)-HTBZ. Paroxetine decreased the clearance of α-HTBZ and β-HTBZ metabolites of AUSTEDO with corresponding increases in mean half-life of approximately 1.5-fold and 2.7-fold, respectively. In the presence of paroxetine, Cmax of α-HTBZ and β-HTBZ were 1.2-fold and 2.2-fold higher, respectively [see Drug Interactions (7.1)].

The effect of moderate or weak CYP2D6 inhibitors such as duloxetine, terbinafine, amiodarone, or sertraline on the exposure of deutetrabenazine and its metabolites has not been evaluated.

Transporters

In vitro studies showed that at clinically relevant concentrations, deutetrabenazine and its active metabolites are not substrates of P-glycoprotein (P-gp) and BCRP transporters. Deutetrabenazine and its active metabolites are unlikely substrates of OATP1B1, OATP1B3, and OCT1.

Effect of AUSTEDO/AUSTEDO XR on Other Drugs

CYP Enzymes

In vitro studies showed that at clinically relevant concentrations, deutetrabenazine, and its active metabolites did not inhibit CYP1A2, CYP2B6, CYP2C8, CYP2C9, CYP2C19, CYP2D6, and CYP3A4 enzymes, and did not induce CYP1A2, CYP2B6, and CYP3A4 enzymes.

Transporters

In vitro studies demonstrated that at clinically relevant concentrations, deutetrabenazine and its active metabolites did not inhibit the following transporters: P-gp, BCRP, BSEP, MATE1, MATE2-K, OAT1, OAT3, OATP1B1, OATP1B3, OCT1, and OCT2.

Minor Metabolites

The deutetrabenazine metabolites, 2-methylpropanoic acid of β-HTBZ (M1) and monohydroxy tetrabenazine (M4), have been evaluated in a panel of in vitro drug-drug interaction studies; the results indicate that M1/M4 are not expected to cause clinically relevant drug interactions.

13 NONCLINICAL TOXICOLOGY

13.1 Carcinogenesis, Mutagenesis, Impairment of Fertility

Carcinogenesis

No carcinogenicity studies were performed with deutetrabenazine.

No increase in tumors was observed in p53+/– transgenic mice treated orally with tetrabenazine at doses of 0, 5, 15, and 30 mg/kg/day for 26 weeks.

Mutagenesis

Deutetrabenazine and its deuterated α-HTBZ and β-HTBZ metabolites were negative in in vitro (bacterial reverse mutation and chromosome aberration in human peripheral blood lymphocytes) assays in the presence or absence of metabolic activation and in the in vivo micronucleus assay in mice.

Impairment of Fertility

The effects of deutetrabenazine on fertility have not been evaluated. Oral administration of deutetrabenazine (doses of 5, 10, or 30 mg/kg/day) to female rats for 3 months resulted in estrous cycle disruption at all doses; the lowest dose tested was similar to the maximum recommended human dose (48 mg/day) on a body surface area (mg/m^2) basis.

Oral administration of tetrabenazine (doses of 5, 15, or 30 mg/kg/day) to female rats prior to and throughout mating, and continuing through day 7 of gestation, resulted in disrupted estrous cyclicity at doses greater than 5 mg/kg/day. No effects on mating and fertility indices or sperm parameters (motility, count, density) were observed when males were treated orally with tetrabenazine at doses of 5, 15 or 30 mg/kg/day prior to and throughout mating with untreated females.

14 CLINICAL STUDIES

The studies described below establishing effectiveness for Huntington’s disease and tardive dyskinesia were conducted with AUSTEDO tablets. The efficacy of AUSTEDO XR is based on a relative bioavailability study comparing AUSTEDO XR tablets administered once daily and AUSTEDO tablets administered twice daily [see Clinical Pharmacology (12.3)].

14.1 Chorea Associated with Huntington’s Disease

The efficacy of AUSTEDO as a treatment for chorea associated with Huntington's disease was established primarily in Study 1, a randomized, double-blind, placebo-controlled, multi-center trial conducted in 90 ambulatory patients with manifest chorea associated with Huntington’s disease. The diagnosis of Huntington’s disease was based on family history, neurological exam, and genetic testing. Treatment duration was 12 weeks, including an 8-week dose titration period and a 4-week maintenance period, followed by a 1-week washout. Patients were not blinded to discontinuation. AUSTEDO was started at 6 mg per day and titrated upward, at weekly intervals, in 6 mg increments until satisfactory treatment of chorea was achieved, intolerable side effects occurred, or until a maximal dose of 48 mg per day was reached. The primary efficacy endpoint was the Total Maximal Chorea Score, an item of the Unified Huntington's Disease Rating Scale (UHDRS). On this scale, chorea is rated from 0 to 4 (with 0 representing no chorea) for 7 different parts of the body. The total score ranges from 0 to 28.

Of the 90 patients enrolled, 87 patients completed the study. The mean age was 54 (range 23 to 74). Patients were 56% male and 92% Caucasian. The mean dose after titration was 40 mg per day. Table 5 and Figure 1 summarize the effects of AUSTEDO on chorea based on the Total Maximal Chorea Score. Total Maximal Chorea Scores for patients receiving AUSTEDO improved by approximately 4.4 units from baseline to the maintenance period (average of Week 9 and Week 12), compared to approximately 1.9 units in the placebo group. The treatment effect of -2.5 units was statistically significant (p<0.0001). The Maintenance Endpoint is the mean of the Total Maximal Chorea Scores for the Week 9 and Week 12 visits. At the Week 13 follow-up visit (1 week after discontinuation of the study medication), the Total Maximal Chorea Scores of patients who had received AUSTEDO returned to baseline (Figure 1).

Table 5: Change from Baseline to Maintenance Therapy in Total Maximal Chorea (TMC)* Score in Patients with Huntington’s Disease Treated with AUSTEDO in Study 1
Motor Endpoint | AUSTEDO N = 45 | Placebo N = 45 | p value
Change in Total Chorea Score* from Baseline to Maintenance Therapy† | -4.4 | -1.9 | <0.0001

*TMC is a subscale of the Unified Huntington's Disease Rating Scale (UHDRS)
†Primary efficacy endpoint

Figure 1: Total Maximal Chorea Score Over Time in Study 1

Figure 2: Distribution of the Change in Total Maximal Chorea Scores in Study 1

Figure 2 shows the distribution of values for the change in Total Maximal Chorea Score in Study 1. Negative values indicate a reduction in chorea and positive numbers indicate an increase in chorea.

A patient-rated global impression of change assessed how patients rated their overall Huntington’s disease symptoms. Fifty-one percent of patients treated with AUSTEDO rated their symptoms as “Much Improved” or “Very Much Improved” at the end of treatment, compared to 20% of placebo-treated patients.

In a physician-rated clinical global impression of change, physicians rated 42% percent of patients treated with AUSTEDO as “Much Improved” or “Very Much Improved” at the end of treatment compared to 13% of placebo-treated patients.

14.2 Tardive Dyskinesia

The efficacy of AUSTEDO in the treatment for tardive dyskinesia was established in two 12‑week, randomized, double-blind, placebo-controlled, multi-center trials conducted in 335 adult ambulatory patients with tardive dyskinesia caused by use of dopamine receptor antagonists. Patients had a history of using a dopamine receptor antagonist (antipsychotics, metoclopramide) for at least 3 months (or 1 month in patients 60 years of age and older). Concurrent diagnoses included schizophrenia/schizoaffective disorder (62%) and mood disorder (33%). With respect to concurrent antipsychotic use, 64% of patients were receiving atypical antipsychotics, 12% were receiving typical or combination antipsychotics, and 24% were not receiving antipsychotics.

The Abnormal Involuntary Movement Scale (AIMS) was the primary efficacy measure for the assessment of tardive dyskinesia severity. The AIMS is a 12-item scale; items 1 to 7 assess the severity of involuntary movements across body regions and these items were used in this study. Each of the 7 items was scored on a 0 to 4 scale, rated as: 0=not present; 1=minimal, may be extreme normal (abnormal movements occur infrequently and/or are difficult to detect); 2=mild (abnormal movements occur infrequently and are easy to detect); 3=moderate (abnormal movements occur frequently and are easy to detect) or 4 =severe (abnormal movements occur almost continuously and/or of extreme intensity). The AIMS total score (sum of items 1 to 7) could thus range from 0 to 28, with a decrease in score indicating improvement.

In Study 1, a 12-week, placebo-controlled, fixed-dose trial, adults with tardive dyskinesia were randomized 1:1:1:1 to 12 mg AUSTEDO, 24 mg AUSTEDO, 36 mg AUSTEDO, or placebo. Treatment duration included a 4-week dose escalation period and an 8-week maintenance period followed by a 1-week washout. The dose of AUSTEDO was started at 12 mg per day and increased at weekly intervals in 6 mg/day increments to a dose target of 12 mg, 24 mg or 36 mg per day. The population (n= 222) was 21 to 81 years old (mean 57 years), 48% male, and 79% Caucasian. In Study 1, the AIMS total score for patients receiving AUSTEDO demonstrated statistically significant improvement, from baseline to Week 12, of 3.3 and 3.2 units for the 36 mg and 24 mg arms, respectively, compared with 1.4 units in placebo (Study 1 in Table 6). The improvements on the AIMS total score over the course of the study are displayed in Figure 3. Data did not suggest substantial differences in efficacy across various demographic groups. The treatment response rate distribution, based on magnitude of AIMS total score from baseline to week 12 is displayed in Figure 4.

The mean changes in the AIMS total score by visit are shown in Figure 3.

In Study 2, a 12-week, placebo-controlled, flexible-dose trial, adults with tardive dyskinesia (n=113) received daily doses of placebo or AUSTEDO, starting at 12 mg per day with increases allowed in 6-mg increments at 1-week intervals until satisfactory control of dyskinesia was achieved, until intolerable side effects occurred, or until a maximal dose of 48 mg per day was reached. Treatment duration included a 6-week dose titration period and a 6-week maintenance period followed by a 1-week washout. The population was 25 to 75 years old (mean 55 years), 48% male, and 70% Caucasian. Patients were titrated to an optimal dose over 6 weeks. The average dose of AUSTEDO after treatment was 38.3 mg per day. There was no evidence suggesting substantial differences in efficacy across various demographic groups. In Study 2, AIMS total score for patients receiving AUSTEDO demonstrated statistically significant improvement by 3.0 units from baseline to endpoint (Week 12), compared with 1.6 units in the placebo group with a treatment effect of -1.4 units. Table 6 summarizes the effects of AUSTEDO on tardive dyskinesia based on the AIMS.

Table 6: Improvement in AIMS Total Score in Patients Treated with AUSTEDO in Study 1 and Study 2
Study | Treatment Group | Primary Efficacy Measure: AIMS Total Score
Study | Treatment Group | Mean Baseline Score (SD) | LS Mean Change from Baseline (SE) | Treatment Effect (95% CI)
Study 1 | AUSTEDO 36 mg*; (n= 55) | 10.1 (3.21) | -3.3 (0.42) | -1.9 (-3.09, -0.79)
Study 1 | AUSTEDO 24 mg; (n= 49) | 9.4 (2.93) | -3.2 (0.45) | -1.8 (-3.00, -0.63)
Study 1 | AUSTEDO 12 mg; (n= 60) | 9.6 (2.40) | -2.1 (0.42) | -0.7 (-1.84, 0.42)
Study 1 | Placebo (n= 58) | 9.5 (2.71) | -1.4 (0.41)
Study 2 | AUSTEDO; (12-48 mg/day)*; (n= 56) | 9.7 (4.14) | -3.0 (0.45) | -1.4 (-2.6, -0.2)
Study 2 | Placebo (n= 57) | 9.6 (3.78) | -1.6 (0.46)

*Dose that was statistically significantly different from placebo after adjusting for multiplicity.

LS Mean = Least-squares mean; SD = Standard deviation; SE = Standard error; CI = 2-sided 95% confidence interval

Figure 3: Least Square Means of Change in AIMS Total Score from Baseline for AUSTEDO Compared to Placebo (Study 1)

SE = Standard error

Figure 4: Percent of Patients with Specified Magnitude of AIMS Total Score Improvement at the End of Week 12 (Study 1)

16 HOW SUPPLIED/STORAGE AND HANDLING

16.1 How Supplied

AUSTEDO XR extended-release tablets are supplied in the following configurations:

Strength | Description | Package Configuration | NDC Code
6 mg | Round, grey-coated tablets, with “Q6” printed in black ink on one side | Bottle with child-resistant cap / 30 count | 68546-470-56
12 mg | Round, blue-coated tablets, with “Q12” printed in black ink on one side | Bottle with child-resistant cap / 30 count | 68546-471-56
18 mg | Round, light grey-coated tablets, with “Q18” printed in black ink on one side | Bottle with child-resistant cap / 30 count | 68546-479-56
24 mg | Round, purple-coated tablets, with “Q24” printed in black ink on one side | Bottle with child-resistant cap / 30 count | 68546-472-56
30 mg | Round, light orange-coated tablets, with “Q30” printed in black ink on one side | Bottle with child-resistant cap / 30 count | 68546-473-56
36 mg | Round, light purple-coated tablets, with “Q36” printed in black ink on one side | Bottle with child-resistant cap / 30 count | 68546-474-56
42 mg | Round, orange-coated tablets, with “Q42” printed in black ink on one side | Bottle with child-resistant cap / 30 count | 68546-475-56
48 mg | Round, pink-coated tablets, with “Q48” printed in black ink on one side | Bottle with child-resistant cap / 30 count | 68546-476-56

AUSTEDO XR Patient Titration Kits are supplied in the following configuration:

Strength | Description | Package Configuration | NDC Code
4-Week Patient Titration Kit
12 mg | Round, blue-coated tablets, with “Q12” printed in black ink on one side | Titration Kit / 28 count; Each Titration Kit contains 1 child-resistant blister pack, containing one foil card with extended-release tablets in the following configuration:; Seven 12 mg tablets taken during Week 1; seven 18 mg tablets taken during Week 2; seven 24 mg tablets taken during Week 3; and seven 30 mg tablets taken during Week 4. | 68546-477-29
18 mg | Round, light grey-coated tablets, with “Q18” printed in black ink on one side | Titration Kit / 28 count; Each Titration Kit contains 1 child-resistant blister pack, containing one foil card with extended-release tablets in the following configuration:; Seven 12 mg tablets taken during Week 1; seven 18 mg tablets taken during Week 2; seven 24 mg tablets taken during Week 3; and seven 30 mg tablets taken during Week 4. | 68546-477-29
24 mg | Round, purple-coated tablets, with “Q24” printed in black ink on one side | Titration Kit / 28 count; Each Titration Kit contains 1 child-resistant blister pack, containing one foil card with extended-release tablets in the following configuration:; Seven 12 mg tablets taken during Week 1; seven 18 mg tablets taken during Week 2; seven 24 mg tablets taken during Week 3; and seven 30 mg tablets taken during Week 4. | 68546-477-29
30 mg | Round, light orange-coated tablets, with “Q30” printed in black ink on one side | Titration Kit / 28 count; Each Titration Kit contains 1 child-resistant blister pack, containing one foil card with extended-release tablets in the following configuration:; Seven 12 mg tablets taken during Week 1; seven 18 mg tablets taken during Week 2; seven 24 mg tablets taken during Week 3; and seven 30 mg tablets taken during Week 4. | 68546-477-29

AUSTEDO tablets are supplied in the following configurations:

Strength | Description | Package Configuration | NDC Code
6 mg | Round, purple-coated tablets, with “SD” over “6” printed in black ink on one side | Bottle with child-resistant cap / 60 count | 68546-170-60
9 mg | Round, blue-coated tablets, with “SD” over “9” printed in black ink on one side | Bottle with child-resistant cap / 60 count | 68546-171-60
12 mg | Round, beige-coated tablets, with “SD” over “12” printed in black ink on one side | Bottle with child-resistant cap / 60 count | 68546-172-60

16.2 Storage

Store at 25°C (77°F); excursions permitted to 15°C to 30°C (59°F to 86°F) [see USP Controlled Room Temperature]. Protect from light and moisture. Dispense in original containers or in tight containers as defined in USP.

17 PATIENT COUNSELING INFORMATION

Advise the patient or caregiver to read the FDA-approved patient labeling (Medication Guide).

Administration Instructions

Instruct patients to swallow AUSTEDO XR or AUSTEDO whole and not to chew, crush, or break AUSTEDO XR or AUSTEDO [see Dosage and Administration (2.1)].

AUSTEDO XR

Advise patients to take AUSTEDO XR with or without food in once-daily doses. Inform patients not to be concerned if they occasionally notice something that looks like a tablet shell in their stool [see Description (11)].

AUSTEDO

Advise patients to take AUSTEDO with food. Advise patients to take daily dosages of 12 mg or higher in two divided doses (twice daily).

Risk of Depression and Suicide in Patients with Huntington’s Disease

Advise patients, their caregivers, and families that AUSTEDO XR and AUSTEDO may increase the risk of depression, worsening depression, and suicidality, and to immediately report any symptoms to a healthcare provider [see Contraindications (4), Warnings and Precautions (5.1)].

Prolongation of the QTc Interval

Inform patients to consult their physician immediately if they feel faint, lose consciousness, or have heart palpitations [see Warnings and Precautions (5.3)]. Advise patients to inform physicians that they are taking AUSTEDO XR or AUSTEDO before any new drug is taken.

Parkinsonism

Inform patients that AUSTEDO XR and AUSTEDO may cause Parkinson-like symptoms, which could be severe. Advise patients to consult their healthcare provider if they experience slight shaking, body stiffness, trouble moving, trouble keeping their balance, or falls [see Warnings and Precautions (5.6)].

Risk of Sedation and Somnolence

Advise patients that AUSTEDO XR and AUSTEDO may cause sedation and somnolence and may impair the ability to perform tasks that require complex motor and mental skills. Until they learn how they respond to a stable dose of AUSTEDO XR or AUSTEDO, patients should be careful doing activities that require them to be alert, such as driving a car or operating machinery [see Warnings and Precautions (5.7)].

Interaction with Alcohol or Other Sedating Drugs

Advise patients that alcohol or other drugs that cause sleepiness will worsen somnolence [see Drug Interactions (7.5)].

Concomitant Medications

Advise patients to notify their physician of all medications they are taking and to consult with their healthcare provider before starting any new medications because of a potential for interactions [see Contraindications (4) and Drug Interactions (7.1, 7.4)].

Manufactured for:
Teva Neuroscience, Inc.
Parsippany, NJ 07054

©2025 Teva Neuroscience, Inc.

AUS-013

AUSTEDO XR U.S. Patent Nos: 8,524,733; 9,550,780; 10,959,996; 11,179,386; 11,357,772; 11,311,488; 11,564,917; 11,446,291; 11,648,244; 11,813,232; 12,016,858

AUSTEDO U.S. Patent Nos: 8,524,733; 9,233,959; 9,296,739; 9,550,780; 9,814,708; 10,959,996; 11,179,386; 11,357,772; 11,564,917; 11,446,291; 11,648,244; 11,666,566; 11,813,232; 12,016,858

MEDICATION GUIDE

AUSTEDO XR® (aw-STED-oh XR)
(deutetrabenazine) extended-release tablets, for oral use

AUSTEDO® (aw-STED-oh)
(deutetrabenazine) tablets, for oral use

What is the most important information I should know about AUSTEDO XR and AUSTEDO?

- AUSTEDO XR and AUSTEDO can cause serious side effects in people with Huntington’s disease, including:
  - depression
  - suicidal thoughts
  - suicidal actions

- Do not start taking AUSTEDO XR or AUSTEDO if you have Huntington’s disease and are depressed (have untreated depression or depression that is not well controlled by medicine) or have suicidal thoughts.

- Pay close attention to any changes, especially sudden changes, in mood, behaviors, thoughts, or feelings. This is especially important when AUSTEDO XR or AUSTEDO is started and when the dose is changed.

Call your healthcare provider right away if you become depressed or have any of the following symptoms, especially if they are new, worse, or worry you:

- feel sad or have crying spells
- lose interest in seeing your friends or doing things you used to enjoy
- sleep a lot more or a lot less than usual
- feel unimportant
- feel guilty
- feel hopeless or helpless
- feel more irritable, angry, or aggressive than usual
- feel more or less hungry than usual or notice a big change in your body weight
- have trouble paying attention
- feel tired or sleepy all the time
- have thoughts about hurting yourself or ending your life

What are AUSTEDO XR and AUSTEDO?

AUSTEDO XR and AUSTEDO are prescription medicines that are used to treat:

- the involuntary movements (chorea) of Huntington’s disease. AUSTEDO XR and AUSTEDO do not cure the cause of the involuntary movements, and it does not treat other symptoms of Huntington’s disease, such as problems with thinking or emotions.
- movements in the face, tongue, or other body parts that cannot be controlled (tardive dyskinesia).

It is not known if AUSTEDO XR and AUSTEDO are safe and effective in children.

Who should not take AUSTEDO XR or AUSTEDO?

Do not take AUSTEDO XR or AUSTEDO if you:

- have Huntington’s disease and are depressed or have thoughts of suicide. See “What is the most important information I should know about AUSTEDO XR and AUSTEDO?”
- have liver problems.
- are taking reserpine. Do not take medicines that contain reserpine with AUSTEDO XR or AUSTEDO. If your healthcare provider plans to switch you from taking reserpine to AUSTEDO XR or AUSTEDO, you must wait at least 20 days after your last dose of reserpine before you start taking AUSTEDO XR or AUSTEDO.
- are taking a monoamine oxidase inhibitor (MAOI) medicine. Do not take an MAOI within 14 days after you stop taking AUSTEDO XR or AUSTEDO. Do not start AUSTEDO XR or AUSTEDO if you stopped taking an MAOI in the last 14 days. Ask your healthcare provider or pharmacist if you are not sure.
- are taking tetrabenazine. If your healthcare provider plans to switch you from tetrabenazine to AUSTEDO XR or AUSTEDO, take your first dose of AUSTEDO XR or AUSTEDO on the day after your last dose of tetrabenazine.
- are taking valbenazine.

Before taking AUSTEDO XR or AUSTEDO, tell your healthcare provider about all of your medical conditions, including if you:

- have emotional or mental problems (for example, depression, nervousness, anxiety, anger, agitation, psychosis, previous suicidal thoughts or suicide attempts).
- have liver disease.
- have an irregular heart rhythm or heartbeat (QT prolongation, cardiac arrhythmia) or a heart problem called congenital long QT syndrome.
- have low levels of potassium or magnesium in your blood (hypokalemia or hypomagnesemia).
- have breast cancer or a history of breast cancer.
- are pregnant or plan to become pregnant. It is not known if AUSTEDO XR or AUSTEDO can harm your unborn baby.
- are breastfeeding or plan to breastfeed. It is not known if AUSTEDO XR or AUSTEDO passes into breast milk.

Tell your healthcare provider about all of the medicines you take, including prescription and over-the-counter medicines, vitamins, and herbal supplements.

Taking AUSTEDO XR or AUSTEDO with certain other medicines may cause side effects. Do not start any new medicines while taking AUSTEDO XR or AUSTEDO without talking to your healthcare provider first.

How should I take AUSTEDO XR or AUSTEDO?

- Take AUSTEDO XR or AUSTEDO exactly as your healthcare provider tells you to take it.
- If you take AUSTEDO XR, take your dose by mouth one time each day, with or without food.
- If you take AUSTEDO, take your dose by mouth and with food. If your dose of AUSTEDO is 12 mg or more each day, take AUSTEDO tablets 2 times a day in equal doses.
- Swallow AUSTEDO XR or AUSTEDO tablets whole with water. Do not chew, crush, or break AUSTEDO XR or AUSTEDO tablets before swallowing. If you cannot swallow AUSTEDO XR or AUSTEDO tablets whole, tell your healthcare provider. You may need a different medicine.
- The AUSTEDO XR tablet shell does not dissolve completely in the body after all the medicine has been released. Sometimes the tablet shell may be seen in your stool. This is normal.
- Your healthcare provider may increase your dose of AUSTEDO XR or AUSTEDO each week for several weeks, until you and your healthcare provider find the right dose for you.
- Tell your healthcare provider if you stop taking AUSTEDO XR or AUSTEDO for more than 1 week. Do not take another dose until you talk to your healthcare provider.

What should I avoid while taking AUSTEDO XR or AUSTEDO?

Sleepiness (sedation) is a common side effect of AUSTEDO XR and AUSTEDO. While taking AUSTEDO XR or AUSTEDO, do not drive a car or operate dangerous machinery until you know how AUSTEDO XR or AUSTEDO affects you. Drinking alcohol and taking other drugs that may also cause sleepiness while you are taking AUSTEDO XR or AUSTEDO may increase any sleepiness caused by AUSTEDO XR and AUSTEDO.

What are the possible side effects of AUSTEDO XR and AUSTEDO?

AUSTEDO XR and AUSTEDO can cause serious side effects, including:

- Depression and suicidal thoughts or actions in people with Huntington’s disease. See “What is the most important information I should know about AUSTEDO XR and AUSTEDO?”

- Irregular heartbeat (QT prolongation). AUSTEDO XR and AUSTEDO increases your chance of having certain changes in the electrical activity in your heart. These changes can lead to a dangerous abnormal heartbeat. Taking AUSTEDO XR or AUSTEDO with certain medicines may increase this chance.

- Neuroleptic Malignant Syndrome (NMS). Call your healthcare provider right away and go to the nearest emergency room if you develop these signs and symptoms that do not have another obvious cause:
  - high fever
  - problems thinking
  - increased sweating
  - stiff muscles
  - very fast or uneven heartbeat

- Restlessness. You may get a condition where you feel a strong urge to move. This is called akathisia.
- Parkinsonism. Symptoms of parkinsonism include: slight shaking, body stiffness, trouble moving, trouble keeping your balance, or falls.

The most common side effects of AUSTEDO in people with Huntington’s disease include:

- sleepiness (sedation)
- diarrhea
- tiredness
- dry mouth

The most common side effects of AUSTEDO in people with tardive dyskinesia include:

- inflammation of the nose and throat (nasopharyngitis)
- problems sleeping (insomnia)

The most common side effects of AUSTEDO XR are expected to be similar to AUSTEDO in people with Huntington's disease or tardive dyskinesia.

These are not all the possible side effects of AUSTEDO XR or AUSTEDO. Call your doctor for medical advice about side effects. You may report side effects to FDA at 1-800-FDA-1088.

How should I store AUSTEDO XR and AUSTEDO?

- Store AUSTEDO XR and AUSTEDO tablets at room temperature between 68°F to 77°F (20°C to 25°C).
- Keep the bottle tightly closed to protect AUSTEDO XR and AUSTEDO from light and moisture.
- Do not throw away the desiccant canister in the bottle until the last dose of AUSTEDO XR or AUSTEDO is taken.

Keep AUSTEDO XR and AUSTEDO and all medicines out of the reach of children.

General information about the safe and effective use of AUSTEDO XR and AUSTEDO.

Medicines are sometimes prescribed for purposes other than those listed in a Medication Guide. Do not use AUSTEDO XR or AUSTEDO for a condition for which it was not prescribed. Do not give AUSTEDO XR or AUSTEDO to other people, even if they have the same symptoms you have. It may harm them. You can ask your pharmacist or healthcare provider for information about AUSTEDO XR and AUSTEDO that is written for health professionals.

What are the ingredients in AUSTEDO XR and AUSTEDO?

AUSTEDO XR:

Active ingredient: deutetrabenazine

Inactive ingredients: ammonium hydroxide, black iron oxide, butyl alcohol, butylated hydroxyanisole, butylated hydroxytoluene, cellulose acetate, hydroxypropyl cellulose, hypromellose, isopropyl alcohol, magnesium stearate, polyethylene glycol, polyethylene glycol 3350, polyethylene oxide, polyvinyl alcohol, propylene glycol, shellac, sodium chloride, talc, titanium dioxide, and FD&C red #40 lake. The 6 mg, 12 mg, 18 mg, 30 mg, 36 mg, and 42 mg extended-release tablets also contain FD&C yellow #6 lake. The 6 mg, 12 mg, 24 mg, and 36 mg extended-release tablets also contain FD&C blue #2 lake. The 18 mg extended-release tablets also contain carmine.

AUSTEDO:

Active ingredient: deutetrabenazine

Inactive ingredients: ammonium hydroxide, black iron oxide, n‑butyl alcohol, butylated hydroxyanisole, butylated hydroxytoluene, magnesium stearate, mannitol, microcrystalline cellulose, polyethylene glycol, polyethylene oxide, polysorbate 80, polyvinyl alcohol, povidone, propylene glycol, shellac, talc, titanium dioxide, and FD&C blue #2 lake. The 6 mg tablets also contain FD&C red #40 lake. The 12 mg tablets also contain FD&C yellow #6 lake.

Manufactured for:
Teva Neuroscience, Inc.
Parsippany, NJ 07054

©2025 Teva Neuroscience, Inc.

AUSMG-011

For more information, go to www.AUSTEDO.com or call 1-888-483-8279.

This Medication Guide has been approved by the U.S. Food and Drug Administration. Revised: February 2025

Package/Label Display Panel

NDC 68546-470-56 ONCE-DAILY
Austedo XR® (deutetrabenazine) extended-release tablets
6 mg
Medication Guide Required: Each time AUSTEDO XR is dispensed, give the patient a Medication Guide. Print Medication Guides at: www.tevausa.com/medguides
30 tablets

Package/Label Display Panel

NDC 68546-471-56 ONCE-DAILY
Austedo XR® (deutetrabenazine) extended-release tablets
12 mg
Medication Guide Required: Each time AUSTEDO XR is dispensed, give the patient a Medication Guide. Print Medication Guides at: www.tevausa.com/medguides
30 tablets

Package/Label Display Panel

NDC 68546-479-56 ONCE-DAILY
Austedo XR® (deutetrabenazine) extended-release tablets
18 mg
Medication Guide Required: Each time AUSTEDO XR is dispensed, give the patient a Medication Guide. Print Medication Guides at: www.tevausa.com/medguides
30 tablets

Package/Label Display Panel

NDC 68546-472-56 ONCE-DAILY
Austedo XR® (deutetrabenazine) extended-release tablets
24 mg
Medication Guide Required: Each time AUSTEDO XR is dispensed, give the patient a Medication Guide. Print Medication Guides at: www.tevausa.com/medguides
30 tablets

Package/Label Display Panel

NDC 68546-473-56 ONCE-DAILY
Austedo XR® (deutetrabenazine) extended-release tablets
30 mg
Medication Guide Required: Each time AUSTEDO XR is dispensed, give the patient a Medication Guide. Print Medication Guides at: www.tevausa.com/medguides
30 tablets

Package/Label Display Panel

NDC 68546-474-56 ONCE-DAILY
Austedo XR® (deutetrabenazine) extended-release tablets
36 mg
Medication Guide Required: Each time AUSTEDO XR is dispensed, give the patient a Medication Guide. Print Medication Guides at: www.tevausa.com/medguides
30 tablets

Package/Label Display Panel

NDC 68546-475-56 ONCE-DAILY
Austedo XR® (deutetrabenazine) extended-release tablets
42 mg
Medication Guide Required: Each time AUSTEDO XR is dispensed, give the patient a Medication Guide. Print Medication Guides at: www.tevausa.com/medguides
30 tablets

Package/Label Display Panel

NDC 68546-476-56 ONCE-DAILY
Austedo XR® (deutetrabenazine) extended-release tablets
48 mg
Medication Guide Required: Each time AUSTEDO XR is dispensed, give the patient a Medication Guide. Print Medication Guides at: www.tevausa.com/medguides
30 tablets

Package/Label Display Panel

NDC 68546-490-52 ONCE-DAILY
Austedo® XR (deutetrabenazine) extended-release tablets
6 mg, 12 mg, 24 mg
Once Daily
Patient Titration Kit
4 WEEKS
Rx Only
Medication Guide Required: Each time AUSTEDO XR is dispensed, give the patient the accompanying Medication Guide.
Print Medication Guides at: www.tevausa.com/medguides Dispense in this sealed carton. Monthly carton contains 42 tablets in 2 child-resistant packs including, 14 grey tablets, each containing 6 mg of deutetrabenazine, 14 blue tablets, each containing 12 mg of deutetrabenazine, and 14 purple tablets, each containing 24 mg of deutetrabenazine.
teva

Package/Label Display Panel

NDC 68546-477-29 ONCE-DAILY
Austedo XR® (deutetrabenazine) extended-release tablets
12 mg, 18 mg, 24 mg, 30 mg
One Tablet, Once-Daily
Patient Titration Kit
4 WEEKS
Rx only
Medication Guide Required: Each time AUSTEDO XR is dispensed, give the patient the accompanying Medication Guide.
Print Medication Guides at: www.tevausa.com/medguides Dispense in this sealed carton. Monthly carton contains 28 tablets in a child-resistant blister pack, including, 7 blue tablets, each containing 12 mg of deutetrabenazine, 7 light grey tablets, each containing 18 mg of deutetrabenazine, 7 purple tablets, each containing 24 mg of deutetrabenazine, 7 light orange tablets, each containing 30 mg of deutetrabenazine.
teva

Package/Label Display Panel

NDC 68546-170-60
Austedo® (deutetrabenazine) tablets
6 mg
Medication Guide Required: Each time AUSTEDO is dispensed, give the patient a Medication Guide.
60 tablets

Package/Label Display Panel

NDC 68546-171-60
Austedo® (deutetrabenazine) tablets
9 mg
Medication Guide Required: Each time AUSTEDO is dispensed, give the patient a Medication Guide.
60 tablets

Package/Label Display Panel

NDC 68546-172-60
Austedo® (deutetrabenazine) tablets
12 mg
Medication Guide Required: Each time AUSTEDO is dispensed, give the patient a Medication Guide.
60 tablets

Package/Label Display Panel

NDC 68546-182-70
AUSTEDO®
(deutetrabenazine) tablets
6 mg, 9 mg, 12 mg
4 Week
Patient Titration Kit
12 mg Starting Dose
SAMPLE – NOT FOR SALE
Rx Only
Medication Guide Required: Each time AUSTEDO is dispensed, give the patient the accompanying Medication Guide.
Dispense in this sealed carton.
Monthly carton contains 70 tablets in 3 child-resistant packs including, 28 purple tablets, each containing 6 mg of deutetrabenazine, 28 blue tablets, each containing 9 mg of deutetrabenazine, and 14 beige tablets, each containing 12 mg of deutetrabenazine.
teva

Package/Label Display Panel

NDC 68546-181-49
Rx Only
Chorea associated with Huntington's disease
4 Week Patient Titration Kit
6 mg Starting Dose
AUSTEDO®(deutetrabenazine) tablets
6 mg, 9 mg, 12 mg

Week | Tablets per day
1 | Take 1 (6 mg) tablet every morning
2 | Take 1 (6 mg) tablet every morning and 1 (6 mg) tablet every evening
3 | Take 1 (9 mg) tablet every morning and 1 (9 mg) tablet every evening
4 | Take 1 (12 mg) tablet every morning and 1 (12 mg) tablet every evening

SAMPLE – NOT FOR SALE
Medication Guide Required: Each time AUSTEDO is dispensed, give the patient the accompanying Medication Guide.
Dispense in this sealed carton.
Monthly carton contains 49 tablets in 2 child-resistant packs including, 21 purple tablets, each containing 6 mg of deutetrabenazine, 14 blue tablets, each containing 9 mg of deutetrabenazine, and 14 beige tablets, each containing 12 mg of deutetrabenazine.
teva

Package/Label Display Panel

NDC 68546-176-28 Rx Only
1 PRESS AND HOLD HERE
Tardive Dyskinesia Titration Pack 12 mg Starting Dose
AUSTEDO® (deutetrabenazine) tablets
6 mg and 9 mg
SAMPLE – NOT FOR SALE
1 Press & hold button 2 Pull out card
Medication Guide Required: Each time AUSTEDO is dispensed, give the patient the accompanying Medication Guide.
1 tablet dispenser containing 28 tablets in the following order:

- Week 1: 14 purple tablets containing 6 mg deutetrabenazine
- Week 2: 14 blue tablets containing 9 mg deutetrabenazine

2 PULL OUT HERE
teva

Package/Label Display Panel

NDC 68546-177-21 Rx Only
1 PRESS AND HOLD HERE
Chorea associated with Huntington's disease Titration Pack 6 mg Starting Dose
AUSTEDO® (deutetrabenazine) tablets
6 mg
SAMPLE – NOT FOR SALE
1 Press & hold button 2 Pull out card
Medication Guide Required: Each time AUSTEDO is dispensed, give the patient the accompanying Medication Guide.
1 tablet dispenser containing 21 tablets in the following order:

- Week 1: 7 purple tablets containing 6 mg deutetrabenazine
- Week 2: 14 purple tablets containing 6 mg deutetrabenazine

2 PULL OUT HERE
teva